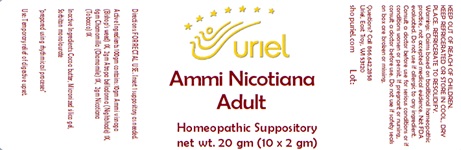 DRUG LABEL: Ammi Nicotiana Adult Size
NDC: 48951-1027 | Form: SUPPOSITORY
Manufacturer: Uriel Pharmacy Inc.
Category: homeopathic | Type: HUMAN OTC DRUG LABEL
Date: 20240110

ACTIVE INGREDIENTS: AMMI VISNAGA FRUIT 1 [hp_X]/1 g; MATRICARIA CHAMOMILLA 1 [hp_X]/1 g; ATROPA BELLADONNA 1 [hp_X]/1 g; TOBACCO LEAF 1 [hp_X]/1 g
INACTIVE INGREDIENTS: COCOA BUTTER; SORBITAN MONOLAURATE; SILICON DIOXIDE

Ammi Nicotiana Adult Size

INDICATIONS AND USAGE

Directions: FOR RECTAL USE.

DOSAGE AND ADMINISTRATION

Insert 1 suppository as needed.

ACTIVE INGREDIENT

Active Ingredients: 100gm contains: 10gm Ammi visnaga (Bishop’s weed) 1X, 6gm Chamomilla (Chamomile) 1X, 2gm Atropa belladonna (Nightshade) 1X, 2gm Nicotiana (Tobacco) 1X

INACTIVE INGREDIENT

Inactive Ingredients: Cocoa butter, Sorbitan monolaurate, Micronized silica gel

"prepared using rhythmical processes"

PURPOSE

Use: Temporary relief of digestive upset.

KEEP OUT OF REACH OF CHILDREN.

WARNINGS

KEEP REFRIGERATED OR STORE IN COOL, DRY PLACE. REFRIGERATE TO RESOLIDIFY.
Warnings: Claims based on traditional homeopathic practice, not accepted medical evidence. Not FDA evaluated. Do not use if allergic to any ingredient. Consult a doctor before use for serious conditions or if conditions worsen or persist. If pregnant or nursing, consult a doctor before use. Do not use if safety seals on box are broken or missing.

Questions? Call 866.642.2858
Uriel, East Troy, WI 53120
shopuriel.com